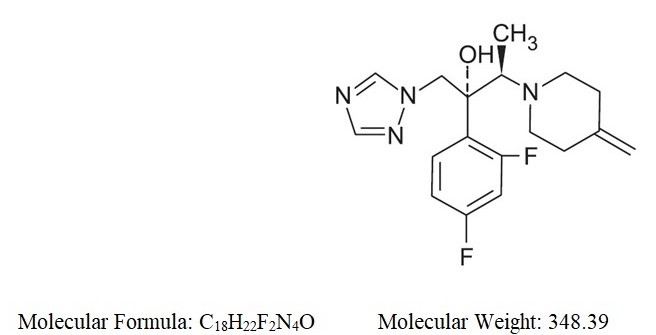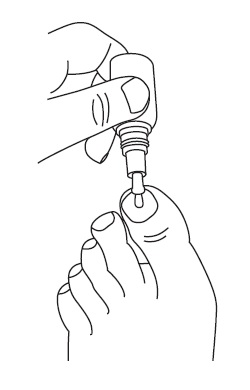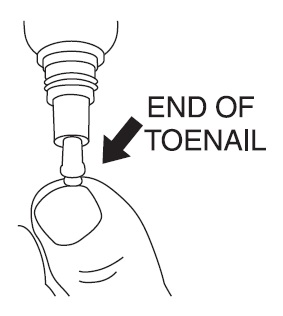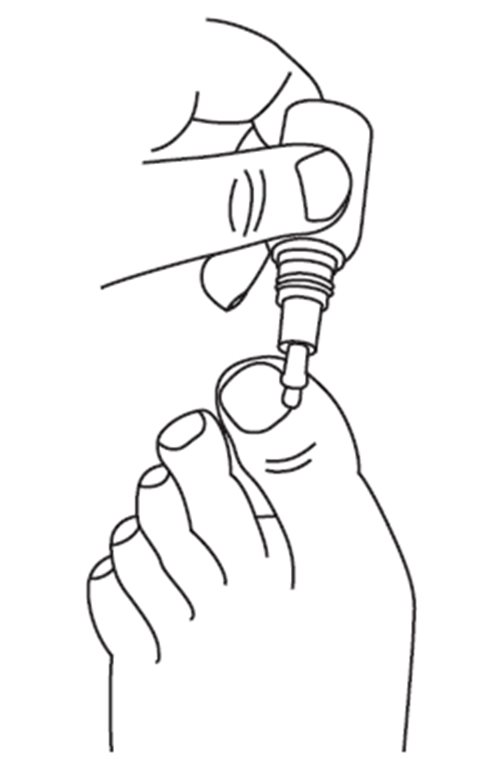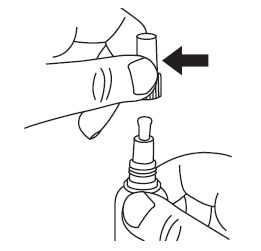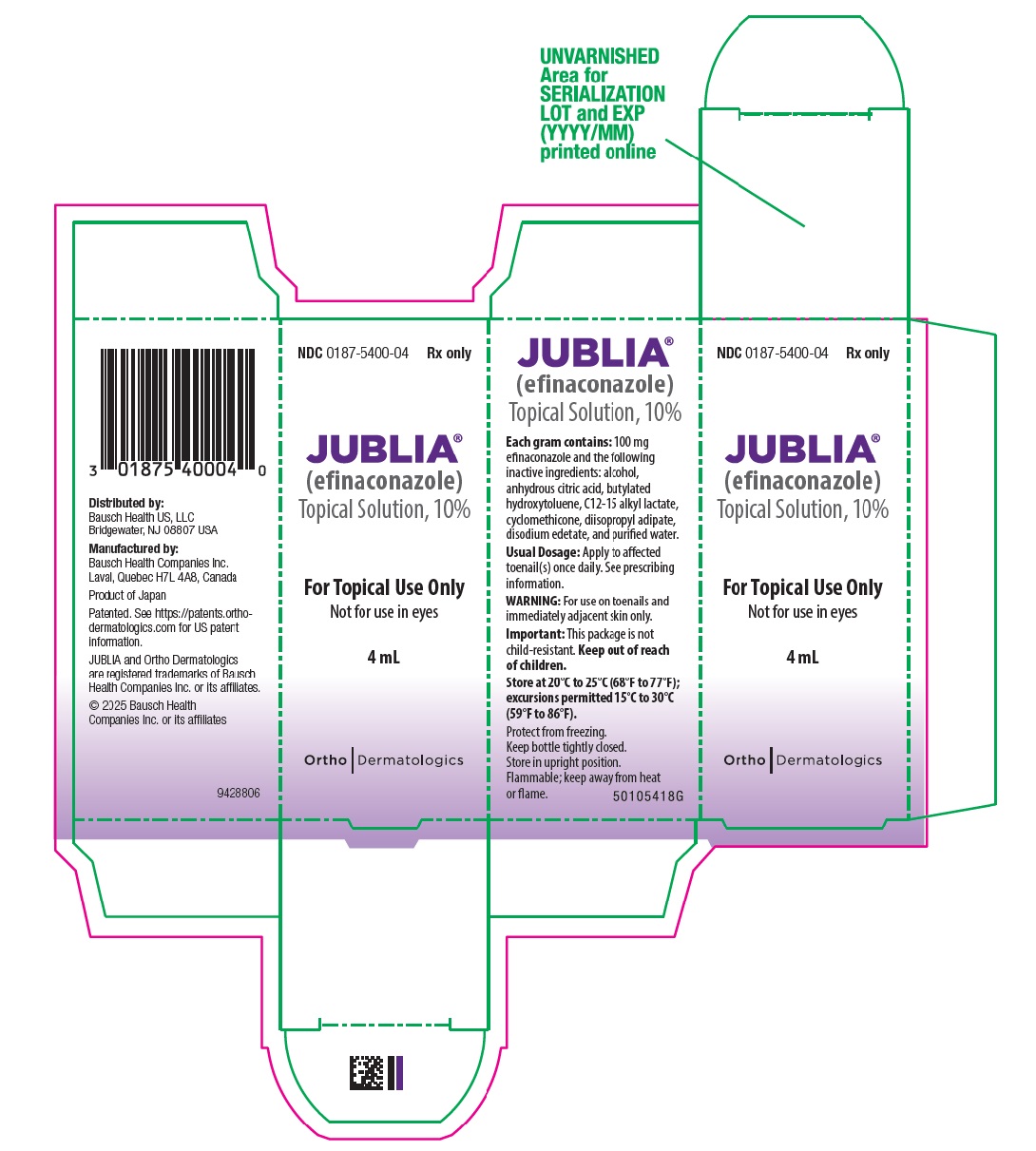 DRUG LABEL: JUBLIA
NDC: 0187-5400 | Form: SOLUTION
Manufacturer: Bausch Health US LLC
Category: prescription | Type: HUMAN PRESCRIPTION DRUG LABEL
Date: 20250701

ACTIVE INGREDIENTS: EFINACONAZOLE 100 mg/1 mL
INACTIVE INGREDIENTS: ALCOHOL; ANHYDROUS CITRIC ACID; BUTYLATED HYDROXYTOLUENE; C12-15 ALKYL LACTATE; CYCLOMETHICONE; DIISOPROPYL ADIPATE; EDETATE DISODIUM; WATER

HIGHLIGHTS OF PRESCRIBING INFORMATION

These highlights do not include all the information needed to use JUBLIA safely and effectively. See full prescribing information for JUBLIA.
JUBLIA® (efinaconazole) topical solution
Initial U.S. Approval: 2014

1 INDICATIONS AND USAGE

JUBLIA is an azole antifungal indicated for the topical treatment of onychomycosis of the toenail(s) due to Trichophyton rubrum and Trichophyton mentagrophytes. (1)

2 DOSAGE AND ADMINISTRATION

- Apply JUBLIA to affected toenails once daily for 48 weeks using the integrated flow-through brush applicator. (2)
- When applying JUBLIA, ensure the toenail, the toenail folds, toenail bed, hyponychium, and the undersurface of the toenail plate, are completely covered. (2)
- For topical use only. Not for oral, ophthalmic, or intravaginal use. (2)

3 DOSAGE FORMS AND STRENGTHS

Solution: 10%. (3)

4 CONTRAINDICATIONS

None. (4)

6 ADVERSE REACTIONS

The most common adverse reactions (incidence >1%) were ingrown toenails, application site dermatitis, application site vesicles, and application site pain. (6.1)

To report SUSPECTED ADVERSE REACTIONS, contact Bausch Health US, LLC at 1-800-321-4576 or FDA at 1-800-FDA-1088 or www.fda.gov/medwatch.

FULL PRESCRIBING INFORMATION

1 INDICATIONS AND USAGE

JUBLIA (efinaconazole) topical solution, 10% is an azole antifungal indicated for the topical treatment of onychomycosis of the toenail(s) due to Trichophyton rubrum and Trichophyton mentagrophytes.

2 DOSAGE AND ADMINISTRATION

Apply JUBLIA to affected toenails once daily for 48 weeks, using the integrated flow-through brush applicator. When applying JUBLIA, ensure the toenail, the toenail folds, toenail bed, hyponychium, and the undersurface of the toenail plate, are completely covered.

JUBLIA is for topical use only and not for oral, ophthalmic, or intravaginal use.

3 DOSAGE FORMS AND STRENGTHS

JUBLIA (efinaconazole) topical solution, 10% contains 100 mg of efinaconazole in each gram of clear, colorless to pale yellow solution.

4 CONTRAINDICATIONS

None.

6 ADVERSE REACTIONS

6.1 Clinical Trials Experience

Because clinical trials are conducted under widely varying conditions, adverse reaction rates observed in the clinical trials of a drug cannot be directly compared to rates in the clinical trials of another drug and may not reflect the rates observed in practice.

In two clinical trials, 1227 subjects were treated with JUBLIA, 1161 for at least 24 weeks and 780 for 48 weeks. Adverse reactions reported within 48 weeks of treatment and in at least 1% of subjects treated with JUBLIA and those reported in subjects treated with the vehicle are presented in Table 1.

Table 1: Adverse Reactions Reported by at Least 1% of Subjects Treated for up to 48 Weeks
Adverse Event, n (%) | JUBLIA (N=1,227) | Vehicle (N=413)
Ingrown toenail | 28 (2.3%) | 3 (0.7%)
Application site dermatitis | 27 (2.2%) | 1 (0.2%)
Application site vesicles | 20 (1.6%) | 0 (0.0%)
Application site pain | 13 (1.1%) | 1 (0.2%)

6.2 Postmarketing Experience

The following adverse reactions have been identified during post-approval use of JUBLIA. Because these reactions are reported voluntarily from a population of uncertain size, it is not always possible to estimate their frequency or establish a causal relationship to drug exposure.

General Disorders and Administration Site Conditions: Application site erythema and exfoliation

Skin and Subcutaneous Tissue Disorders: Onychomadesis, Nail discoloration

7 DRUG INTERACTIONS

In vitro studies have shown that JUBLIA, at therapeutic concentrations, neither inhibits nor induces cytochrome P450 (CYP450) enzymes.

8 USE IN SPECIFIC POPULATIONS

8.1 Pregnancy

Risk Summary

There are no available human data for the use of JUBLIA during pregnancy to inform any drug associated risks of major birth defects, miscarriage, or adverse maternal or fetal outcomes.

In animal reproduction studies, efinaconazole did not cause malformations or any harm to the fetus when administered to pregnant rabbits and rats during the period of organogenesis at subcutaneous doses up to 112 and 154 times, respectively, the Maximum Recommended Human Dose (MRHD) based on Area Under the Curve (AUC) comparisons. Embryolethality was observed only in rats in the presence of maternal toxicity at systemic exposures 559 times the MRHD based on AUC comparisons. Subcutaneous efinaconazole administration to pregnant rats from the beginning of organogenesis through the end of lactation did not cause embryofetal toxicity or developmental effects at systemic exposures 17 times the MRHD based on AUC comparisons (see Data).

The background risk of major birth defects and miscarriage for the indicated population is unknown. However, the background risk in the U.S. general population of major birth defects is 2 to 4%, and of miscarriage is 15 to 20%, of clinically recognized pregnancies.

Data

Animal Data

Systemic embryofetal development studies were conducted in rats and rabbits. Subcutaneous doses of 2, 10 and 50 mg/kg/day efinaconazole were administered during the period of organogenesis (gestational days 6-16) to pregnant female rats. In the presence of maternal toxicity, embryofetal toxicity (increased embryofetal deaths, decreased number of live fetuses, and placental effects) was noted at 50 mg/kg/day (559 times the MRHD based on AUC comparisons). No embryofetal toxicity was noted at 10 mg/kg/day (112 times the MRHD based on AUC comparisons). No malformations were observed at 50 mg/kg/day (559 times the MRHD based on AUC comparisons).

Subcutaneous doses of 1, 5, and 10 mg/kg/day efinaconazole were administered during the period of organogenesis (gestational days 6-19) to pregnant female rabbits. In the presence of maternal toxicity, there was no embryofetal toxicity or malformations at 10 mg/kg/day (154 times the MRHD based on AUC comparisons).

In a pre- and postnatal development study in rats, subcutaneous doses of 1, 5 and 25 mg/kg/day efinaconazole were administered from the beginning of organogenesis (gestation day 6) through the end of lactation (lactation day 20). In the presence of maternal toxicity, embryofetal toxicity (increased prenatal pup mortality, reduced live litter sizes and increased postnatal pup mortality) was noted at 25 mg/kg/day. No embryofetal toxicity was noted at 5 mg/kg/day (17 times the MRHD based on AUC comparisons). No effects on postnatal development were noted at 25 mg/kg/day (89 times the MRHD based on AUC comparisons).

8.2 Lactation

Risk Summary

It is not known whether efinaconazole is excreted in human milk. After repeated subcutaneous administration, efinaconazole was detected in milk of nursing rats. Because many drugs are excreted in human milk, caution should be exercised when JUBLIA is administered to nursing women.

The developmental and health benefits of breastfeeding should be considered, along with the mother’s clinical need for JUBLIA, and any potential adverse effects on the breastfed infant from JUBLIA.

8.4 Pediatric Use

The safety and effectiveness of JUBLIA were established in patients 6 years and older. Use of JUBLIA in these age groups is supported by evidence from well-controlled trials in adults with additional data from an open-label safety study in 60 pediatric subjects ages 6 to 17 (including a pharmacokinetic study in 17 subjects 12 years to less than 17 years old) [see Clinical Pharmacology (12.3)]. Safety and effectiveness of JUBLIA in pediatric subjects under 6 years of age have not been established.

8.5 Geriatric Use

Of the total number of subjects in clinical trials of JUBLIA, 11.3% were 65 and over, while none were 75 and over. No overall differences in safety and effectiveness were observed between these subjects and younger subjects, and other reported clinical experience has not identified differences in responses between the elderly and the younger subjects, but greater sensitivity of some older individuals cannot be ruled out.

11 DESCRIPTION

JUBLIA (efinaconazole) topical solution, 10% is a clear, colorless to pale yellow solution for topical use. Each gram of JUBLIA contains 100 mg of efinaconazole. Efinaconazole is an azole antifungal with a chemical name of ((2R,3R)-2-(2,4-difluorophenyl)-3-(4-methylenepiperidin-1-yl)-1-(1H-1,2,4-triazol-1-yl) butan-2-ol). The structural formula for efinaconazole is represented below:

JUBLIA contains the following inactive ingredients: alcohol, anhydrous citric acid, butylated hydroxytoluene, C12-15 alkyl lactate, cyclomethicone, diisopropyl adipate, disodium edetate, and purified water.

12 CLINICAL PHARMACOLOGY

12.1 Mechanism of Action

JUBLIA topical solution is an azole antifungal [see Clinical Pharmacology (12.4)].

12.2 Pharmacodynamics

The pharmacodynamics of JUBLIA is unknown.

12.3 Pharmacokinetics

Systemic absorption of efinaconazole in 18 adult subjects with severe onychomycosis was determined after application of JUBLIA once daily for 28 days to patients’ 10 toenails and 0.5 cm adjacent skin. The concentration of efinaconazole in plasma was determined at multiple time points over the course of 24-hour periods on days 1, 14, and 28. Efinaconazole mean ± SD plasma Cmax on Day 28 was 0.67 ± 0.37 ng/mL and the mean ± SD AUC was 12.15 ± 6.91 ng*h/mL. The plasma concentration versus time profile at steady state was generally flat over a 24-hour dosing interval. In a separate study of healthy volunteers, the plasma half-life of efinaconazole following daily applications when applied to all 10 toenails for 7 days was 29.9 hours.

Specific Populations

Pediatric patients

PK of efinaconazole was assessed in 17 pediatric subjects 12 to <17 years of age with moderate to severe onychomycosis following application of JUBLIA once daily to all 10 toenails for 28 days.

The plasma concentrations of efinaconazole in pediatric subjects were relatively flat over a 24-hour dosing interval. The mean ± SD plasma Cmax and AUC0-24 for efinaconazole on Day 28 were 0.55±0.38 ng/mL and 11.4±7.68 h•ng/mL, respectively.

Drug Interactions

JUBLIA is considered a non-inhibitor of the CYP450 enzyme family. In in vitro studies using human liver microsomes, efinaconazole did not inhibit CYP1A2, CYP2A6, CYP2C8, CYP2C9, CYP2C19, CYP2D6, CYP2PE1 and CYP3A4 enzyme activities at expected clinical systemic concentrations. In vitro studies in human primary hepatocytes showed that efinaconazole did not induce CYP1A2 or CYP3A4 activities.

12.4 Microbiology

Mechanism of Action

Efinaconazole is an azole antifungal. Efinaconazole inhibits fungal lanosterol 14α-demethylase involved in the biosynthesis of ergosterol, a constituent of fungal cell membranes.

Activity In Vitro and In Vivo

Efinaconazole has been shown to be active against isolates of the following microorganisms, both in vitro and in clinical infections. Efinaconazole exhibits in vitro minimum inhibitory concentrations (MICs) of 0.06 mcg/mL or less against most (≥90%) isolates of the following microorganisms:

Trichophyton rubrum

Trichophyton mentagrophytes

Mechanism of Resistance

Efinaconazole drug resistance development was studied in vitro against T. mentagrophytes, T. rubrum and C. albicans. Serial passage of fungal cultures in the presence of sub-growth inhibitory concentrations of efinaconazole increased the MIC by up to 4-fold. The clinical significance of these in vitro results is unknown.

13 NONCLINICAL TOXICOLOGY

13.1 Carcinogenesis, Mutagenesis, Impairment of Fertility

A 2-year dermal carcinogenicity study in mice was conducted with daily topical administration of 3%, 10% and 30% efinaconazole solution. Severe irritation was noted at the treatment site in all dose groups, which was attributed to the vehicle and confounded the interpretation of skin effects by efinaconazole. The high dose group was terminated at Week 34 due to severe skin reactions. No drug-related neoplasms were noted at doses up to 10% efinaconazole solution (248 times the MRHD based on AUC comparisons).

Efinaconazole revealed no evidence of mutagenic or clastogenic potential based on the results of two in vitro genotoxicity tests (Ames assay and Chinese hamster lung cell chromosome aberration assay) and one in vivo genotoxicity test (mouse peripheral reticulocyte micronucleus assay).

No effects on fertility were observed in male and female rats that were administered subcutaneous doses up to 25 mg/kg/day efinaconazole (279 times the MRHD based on AUC comparisons) prior to and during early pregnancy. Efinaconazole delayed the estrous cycle in females at 25 mg/kg/day but not at 5 mg/kg/day (56 times MRHD based on AUC comparisons).

14 CLINICAL STUDIES

The safety and efficacy of once daily use of JUBLIA for the treatment of onychomycosis of the toenail were assessed in two 52-week prospective, multicenter, randomized, double-blind clinical trials in subjects 18 years and older (18 to 70 years of age) with 20% to 50% clinical involvement of the target toenail, without dermatophytomas or lunula (matrix) involvement. The trials compared 48 weeks of treatment with JUBLIA to the vehicle solution. The Complete Cure rate was assessed at Week 52 (4 weeks after completion of therapy). Complete cure was defined as 0% involvement of the target toenail (no clinical evidence of onychomycosis of the target toenail) in addition to Mycologic Cure, defined as both negative fungal culture and negative KOH. Table 2 lists the efficacy results for trials 1 and 2.

Table 2: Efficacy Endpoints

 | Trial 1 |  | Trial 2
 | JUBLIA | Vehicle | JUBLIA | Vehicle
 | (N=656) | (N=214) | (N=580) | (N=201)
Complete Curea | 117 17.8% | 7 3.3% | 88 15.2% | 11 5.5%
Complete or Almost Complete Cureb | 173 26.4% | 15 7.0% | 136 23.4% | 15 7.5%
Mycologic Curec | 362 55.2% | 36 16.8% | 310 53.4% | 34 16.9%
a Complete cure defined as 0% clinical involvement of the target toenail plus negative KOH and negative culture.
b Complete or almost complete cure defined as ≤5% affected target toenail area involved and negative KOH and culture.
c Mycologic cure defined as negative KOH and negative culture.

16 HOW SUPPLIED/STORAGE AND HANDLING

JUBLIA (efinaconazole) topical solution, 10% is a clear, colorless to pale yellow solution supplied in a white plastic bottle with an integrated flow-through brush applicator as follows:

- 4 mL (NDC 0187-5400-04)
- 8 mL (NDC 0187-5400-08)

Storage and Handling Conditions:

Store at 20°C to 25°C (68°F to 77°F); excursions permitted to 15°C to 30°C (59°F to 86°F) [see USP Controlled Room Temperature].

- Solution is flammable; keep away from heat or flame.
- Protect from freezing.
- Keep out of reach of children.
- Keep bottle tightly closed.
- Store in upright position.

17 PATIENT COUNSELING INFORMATION

Advise the patient to read the FDA-approved patient labeling (Patient Information and Instructions for Use).

- JUBLIA is for external use only and is not for oral, ophthalmic, or intravaginal use. It is for use on toenails and immediately adjacent skin only.
- Apply JUBLIA once daily to clean dry toenails. Wait for at least 10 minutes after showering, bathing, or washing before applying.
- Use JUBLIA only on the affected toenails, as directed by your healthcare provider.
- Inform a healthcare professional if the area of application shows signs of persistent irritation (for example, redness, itching, swelling).
- The impact of nail polish or other cosmetic nail products on the efficacy of JUBLIA has not been evaluated.
- Flammable, avoid use near heat or open flame.

Distributed by:
Bausch Health US, LLC
Bridgewater, NJ 08807 USA

Manufactured by:
Bausch Health Companies Inc.
Laval, Quebec H7L 4A8, Canada

Patented. See https://patents.ortho-dermatologics.com for US patent information.

JUBLIA is a registered trademark of Bausch Health Companies Inc. or its affiliates.

© 2025 Bausch Health Companies Inc. or its affiliates

9462906

PATIENT INFORMATION
JUBLIA® (joo-blee-uh)
(efinaconazole) topical solution, 10%

Important information: JUBLIA is for use on toenails and surrounding skin only. Do not use JUBLIA in your mouth, eyes, or vagina.

What is JUBLIA?
JUBLIA is a prescription medicine used to treat fungal infections of the toenails.
It is not known if JUBLIA is safe and effective for use in children under 6 years of age.

What should I tell my healthcare provider before using JUBLIA?
Before you use JUBLIA, tell your healthcare provider about all your medical conditions, including if you:

- are pregnant or plan to become pregnant. It is not known if JUBLIA can harm your unborn baby.
- are breastfeeding or plan to breastfeed. It is not known if JUBLIA passes into your breast milk.

Tell your healthcare provider about all the medicines you take, including prescription and over-the-counter medicines, vitamins, and herbal supplements.

How should I use JUBLIA?

See the “Instructions for Use” for detailed information about the right way to use JUBLIA.

- Use JUBLIA exactly as your healthcare provider tells you to use it.
- Apply JUBLIA to your affected toenails 1 time each day. Wait for at least 10 minutes after showering, bathing, or washing before applying JUBLIA.
- JUBLIA is used for 48 weeks.
- It is not known if the use of nail polish or other cosmetic nail products (such as gel nails or acrylic nails) will affect how JUBLIA works.

What should I avoid while using JUBLIA?

- JUBLIA is flammable. Avoid heat and flame while applying JUBLIA to your toenail.

What are the possible side effects of JUBLIA?

JUBLIA may cause irritation at the treated site. The most common side effects include: ingrown toenail, redness, itching, swelling, burning or stinging, blisters, and pain. Tell your healthcare provider if you have any side effects that bother you or that do not go away.

These are not all the possible side effects of JUBLIA.

Call your doctor for medical advice about side effects. You may report side effects to the FDA at 1‑800-FDA-1088.

How should I store JUBLIA?

- Store JUBLIA at room temperature, between 68°F to 77°F (20°C to 25°C). Do not freeze JUBLIA.
- Keep the bottle tightly closed and store in upright position.
- JUBLIA is flammable. Keep away from heat and flame.
  Keep JUBLIA and all medicines out of reach of children.

General information about the safe and effective use of JUBLIA

Medicines are sometimes prescribed for purposes other than those listed in a Patient Information leaflet. You can ask your pharmacist or healthcare provider for information about JUBLIA that is written for healthcare professionals. Do not use JUBLIA for a condition for which it was not prescribed. Do not give JUBLIA to other people, even if they have the same condition you have. It may harm them.

What are the ingredients in JUBLIA?

Active ingredients: efinaconazole

Inactive ingredients: alcohol, anhydrous citric acid, butylated hydroxytoluene, C12-15 alkyl lactate, cyclomethicone, diisopropyl adipate, disodium edetate, and purified water.

Distributed by: Bausch Health US, LLC, Bridgewater, NJ 08807 USA

Manufactured by: Bausch Health Companies Inc., Laval, Quebec H7L 4A8, Canada

Patented. See https://patents.ortho-dermatologics.com for US patent information.

JUBLIA is a registered trademark of Bausch Health Companies Inc. or its affiliates.

© 2025 Bausch Health Companies Inc. or its affiliates

For more information, call 1-800-321-4576.

This Patient Information has been approved by the U.S. Food and Drug Administration. Revised: 07/2025 9462906

INSTRUCTIONS FOR USE

JUBLIA® (joo-blee-uh)

(efinaconazole)

topical solution, 10%

Important information: JUBLIA is for use on toenails and surrounding skin only. Do not use JUBLIA in your mouth, eyes or vagina.

Read this Instructions for Use that comes with JUBLIA before you start using it. Talk to your healthcare provider if you have any questions.

How to apply JUBLIA:

Your toenails should be clean and dry before you apply JUBLIA. Wait at least 10 minutes after showering, bathing, or washing before applying JUBLIA.

Step 1: Remove the cap from the JUBLIA bottle.

Step 2: Prepare JUBLIA for application.

- Hold the JUBLIA bottle upside down directly over the affected toenail and gently squeeze the bottle to moisten the entire brush with the solution.

Step 3: Apply JUBLIA
2. While holding the bottle upside down, use the moistened brush to apply JUBLIA by brushing it gently onto the affected toenail(s). Gently squeeze the JUBLIA bottle to moisten the brush if needed.
3. Gently spread JUBLIA over the entire toenail around the cuticle, folds of the skin next to the sides of the toenail, and underneath the end of the toenail.
4. Do not squeeze bottle while spreading JUBLIA.
Do not press or rub the brush firmly against the toenail.

Step 4: For the big toenail, repeat Step 3 to apply JUBLIA a second time.

Step 5: After applying JUBLIA, the entire toenail and surrounding skin should be covered with the solution. Let the treated area dry completely before covering it with bedding, socks, or other clothing.

Step 6: Replace the cap tightly on the bottle.

Step 7: Wash your hands with soap and water after applying JUBLIA.

How should I store JUBLIA?

- Store JUBLIA at room temperature, between 68°F to 77°F (20°C to 25°C). Do not freeze JUBLIA.
- Keep the bottle tightly closed and store in an upright position.
- JUBLIA is flammable. Keep away from heat and flame.

Keep JUBLIA and all medicines out of the reach of children.

Distributed by: Bausch Health US, LLC, Bridgewater, NJ 08807 USA

Manufactured by: Bausch Health Companies Inc., Laval, Quebec H7L 4A8, Canada

Patented. See https://patents.ortho-dermatologics.com for US patent information.

JUBLIA is a registered trademark of Bausch Health Companies Inc. or its affiliates.

© 2025 Bausch Health Companies Inc. or its affiliates

This Instructions for Use has been approved by the US Food and Drug Administration.

Revised: 07/2025 9462906

PACKAGE LABEL

-------------------------------------------------------
REPRESENTATIVE PACKAGING

NDC 0187-5400-04

Rx only

JUBLIA®
(efinaconazole)
Topical Solution, 10%

For Topical Use Only
Not for use in eyes

4 mL

Ortho Dermatologics